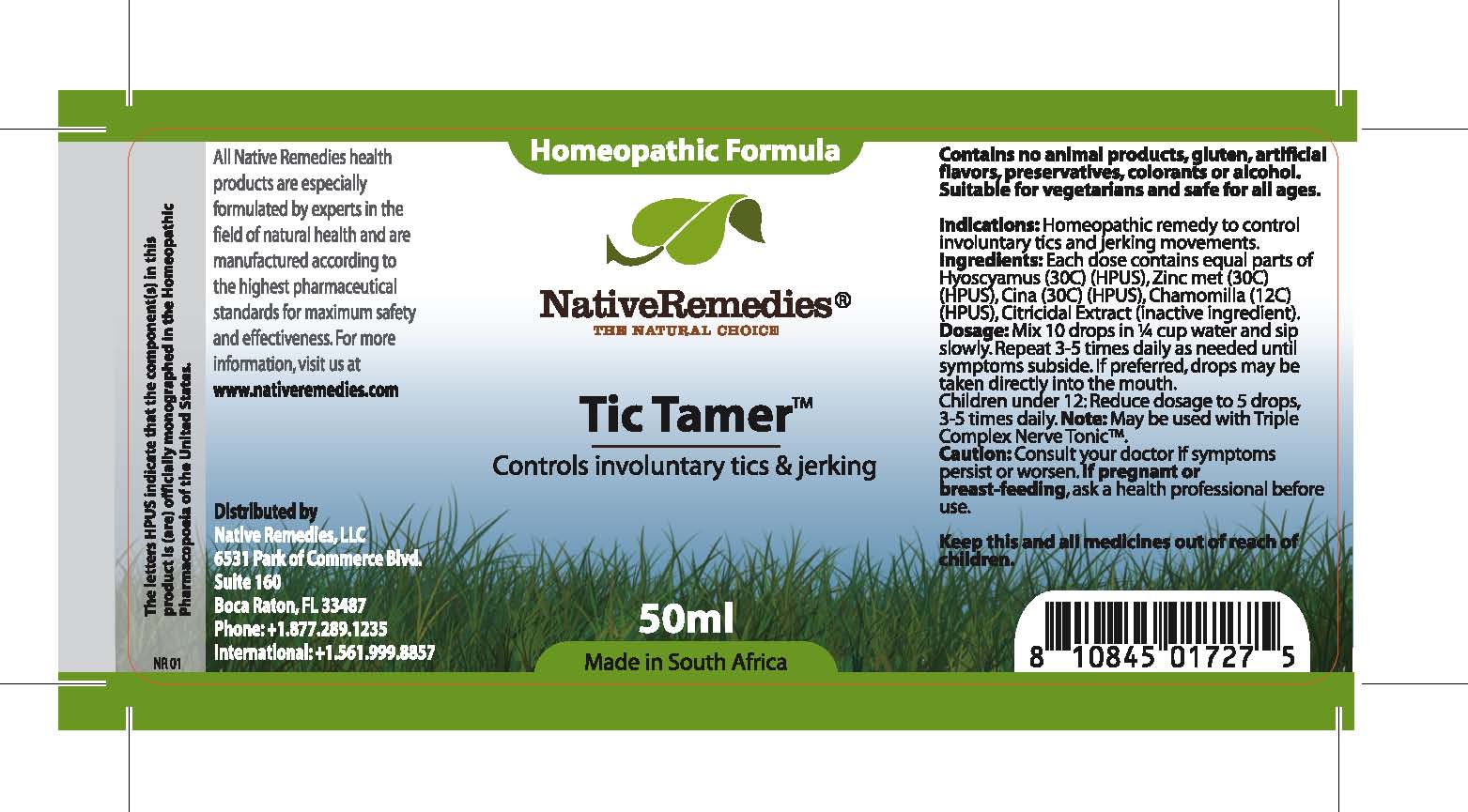 DRUG LABEL: Tic Tamer
NDC: 68647-175 | Form: TINCTURE
Manufacturer: Feelgood Health
Category: homeopathic | Type: HUMAN OTC DRUG LABEL
Date: 20100616

ACTIVE INGREDIENTS: HYOSCYAMUS 30 [hp_C]/50 mg; ZINC METHIONINE SULFATE 30 [hp_C]/50 mg; ARTEMISIA CINA FLOWER 30 [hp_C]/50 mg; CHAMOMILE 12 [hp_C]/50 mg
INACTIVE INGREDIENTS: GRAPEFRUIT SEED 1 1/0.025 mg; WATER 1 1/989.75 mg

TIC TAMER

DESCRIPTION

Controls involuntary tics and jerking

INDICATIONS AND USAGE

Indications: Homeopathic remedy to controlinvoluntary tics and jerking movements.

DOSAGE AND ADMINISTRATION

Dosage: Mix 10 drops in ¼ cup water and sip slowly. Repeat 3-5 times daily as needed until symptoms subside. If preferred, drops may be taken directly into the mouth. Children under 12: Reduce dosage to 5 drops, 3-5 times daily. May be used with Triple Complex Nerve Tonic™.

GENERAL PRECAUTIONS

Caution: Consult your doctor if symptoms persist or worsen. Keep this and all medicines out of reach of children.

ACTIVE INGREDIENT

Ingredients: Each dose contains equal parts of Hyoscyamus (30C) (HPUS), Zinc met (30C) (HPUS), Cina (30C) (HPUS), Chamomilla (12C) (HPUS)

Citricidal Extract (inactive ingredient).

PREGNANCY

If pregnant or breastfeeding, ask a health professional before use

USER SAFETY WARNINGS

Contains no animal products, gluten, artificial flavors, preservatives, colorants or alcohol. Suitable for vegetarians and safe for all ages.

PATIENT COUNSELING INFORMATION

All Native Remedies health products are especially formulated by experts in the field of natural health and are manufactured according to the highest pharmaceutical standards for maximum safety and effectiveness. For more information, visit us at www.nativeremedies.com

Distributed by

Native Remedies, LLC

6531 Park of Commerce Blvd.

Suite 160

Boca Raton, FL 33487

Phone: +1.877.289.1235

International: +1.561.999.8857

The letters HPUS indicate that the component(s) in this product is (are) officially monographed in the Homeopathic Pharmacopoeia of the United States.